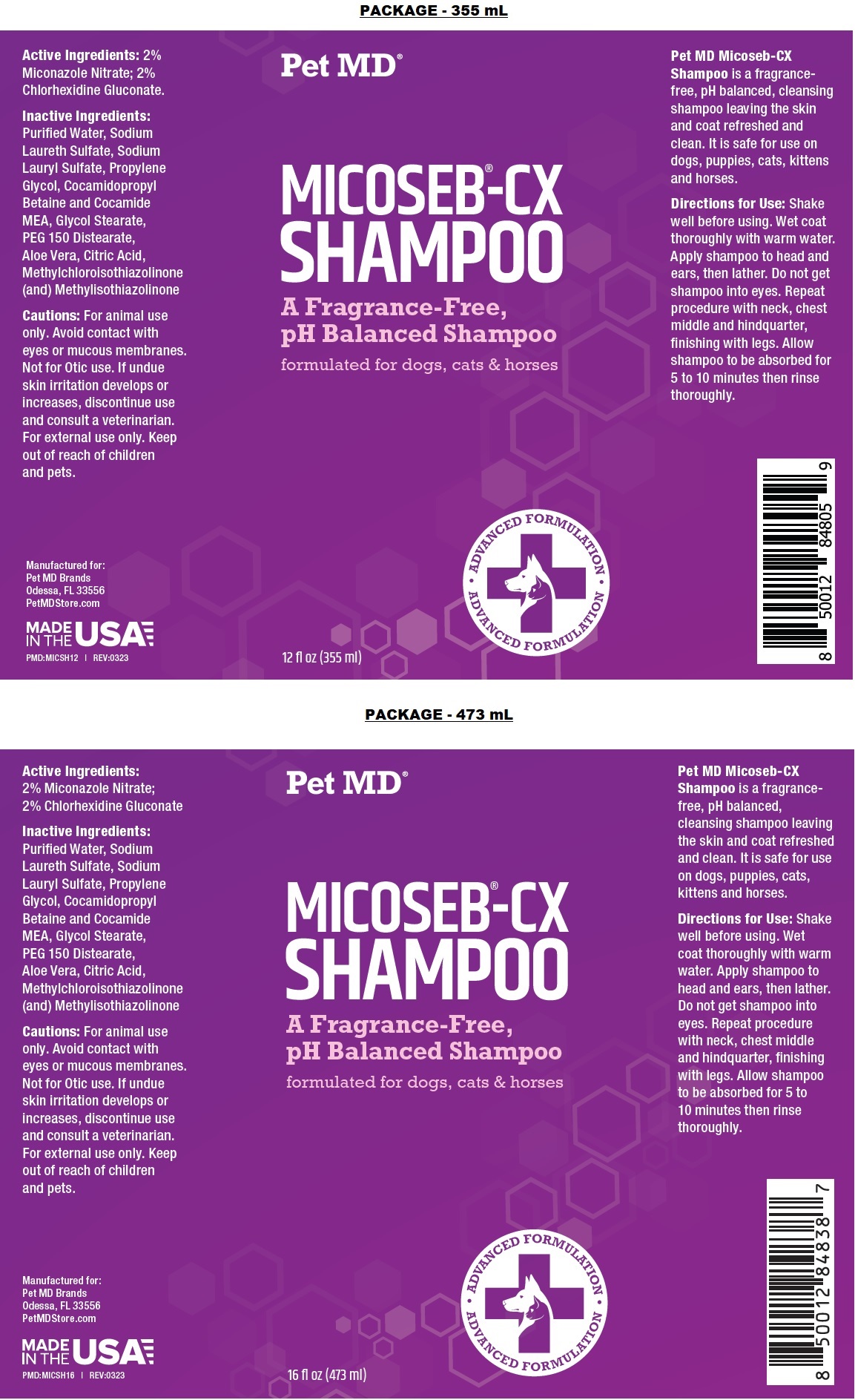 DRUG LABEL: Pet MD Micoseb
NDC: 86090-013 | Form: SHAMPOO
Manufacturer: Pet MD Brands, LLC
Category: animal | Type: OTC ANIMAL DRUG LABEL
Date: 20230908

ACTIVE INGREDIENTS: MICONAZOLE NITRATE 2 g/100 mL; CHLORHEXIDINE GLUCONATE 2 g/100 mL
INACTIVE INGREDIENTS: WATER; SODIUM LAURETH-3 SULFATE; SODIUM LAURYL SULFATE; PROPYLENE GLYCOL; COCAMIDOPROPYL BETAINE; COCO MONOETHANOLAMIDE; GLYCOL STEARATE; PEG-150 DISTEARATE; ALOE VERA LEAF; CITRIC ACID MONOHYDRATE; METHYLCHLOROISOTHIAZOLINONE; METHYLISOTHIAZOLINONE

Pet MD® MICOSEB®-CX SHAMPOO

Active Ingredients:

2% Miconazole Nitrate; 2% Chlorhexidine Gluconate.

INDICATIONS AND USAGE

Pet MD Micoseb-CX Shampoo is a fragrance-free, pH balanced, cleansing shampoo leaving the skin and coat refreshed and clean. It is safe for use on dogs, puppies, cats, kittens and horses.

Inactive Ingredients:

Purified Water, Sodium Laureth Sulfate, Sodium Lauryl Sulfate, Propylene Glycol, Cocamidopropyl Betaine and Cocamide MEA, Glycol Stearate, PEG 150 Distearate, Aloe Vera, Citric Acid, Methylchloroisothiazolinone (and) Methylisothiazolinone

Cautions:

For animal use only. Avoid contact with eyes or mucous membranes. Not for Otic use. If undue skin irritation develops or increases, discontinue use and consult a veterinarian. For external use only. Keep out of reach of children and pets.

Directions for Use:

Shake well before using. Wet coat thoroughly with warm water. Apply shampoo to head and ears, then lather. Do not get shampoo into eyes. Repeat procedure with neck, chest middle and hindquarter, finishing with legs. Allow shampoo to be absorbed for 5 to 10 minutes then rinse thoroughly.

formulated for dogs, cats & horses

ADVANCED FORMULATION

Manufactured for:
Pet MD Brands
Odessa, FL 33556
PetMDStore.com

MADE IN THE USA